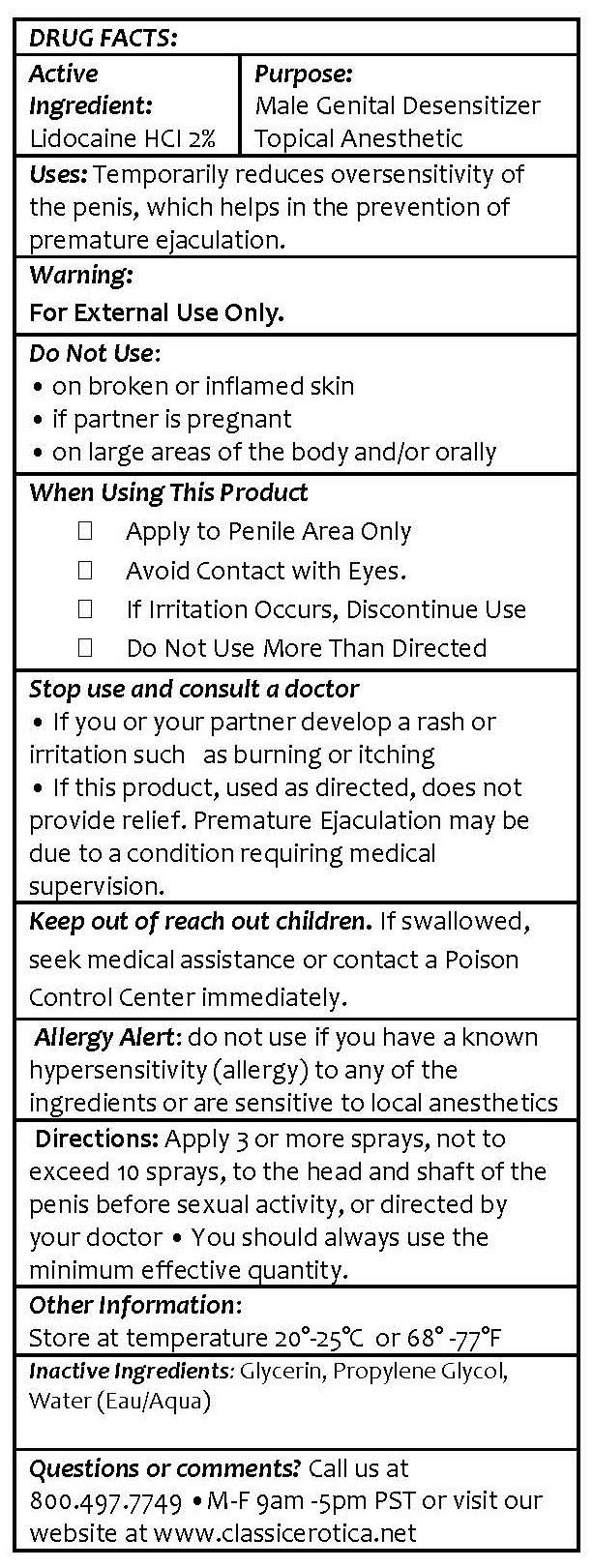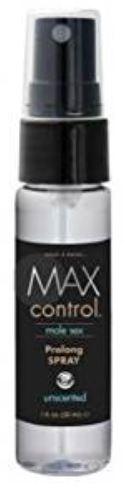 DRUG LABEL: MAX 4 MEN - MAX CONTROL MALE SEX PROLONG
NDC: 60886-102 | Form: SPRAY
Manufacturer: WTFN INC. DBA CLASSIC EROTICA
Category: otc | Type: HUMAN OTC DRUG LABEL
Date: 20180325

ACTIVE INGREDIENTS: LIDOCAINE 2 g/100 mL
INACTIVE INGREDIENTS: GLYCERIN; PROPYLENE GLYCOL; Water

CLASSIC EROTICA - MAX 4 MEN - MAX CONTROL MALE SEX PROLONG SPRAY - UNSCENTED

ACTIVE INGREDIENT:

Lidocaine HCI 2%

PURPOSE:

Male Genital Desensitizer
Topical Anesthetic

USES:

Temporarily reduces oversensitivity of the penis, which helps in the prevention of premature ejaculation.

WARNING:

For External Use Only.

Do Not Use:
• on broken or inflamed skin
• if partner is pregnant
• on large areas of the body and/or orally

When Using This Product

- Apply to Penile Area Only
- Avoid Contact with Eyes.
- If Irritation Occurs, Discontinue Use
- Do Not Use More Than Directed

Stop use and consult a doctor
• If you or your partner develop a rash or irritation such as burning or itching
• If this product, used as directed, does not provide relief. Premature Ejaculation may be due to a condition requiring medical supervision.

KEEP OUT OF REACH OF CHILDREN

Keep out of reach out children. If swallowed, seek medical assistance or contact a Poison Control Center immediately.

Allergy Alert: do not use if you have a known hypersensitivity (allergy) to any of the ingredients or are sensitive to local anesthetics

DIRECTIONS:

Apply 3 or more sprays, not to exceed 10 sprays, to the head and shaft of the penis before sexual activity, or directed by your doctor • You should always use the minimum effective quantity.

OTHER INFORMATION:

Store at temperature 20°-25° C or 68° -77° F

INACTIVE INGREDIENTS:

Glycerin, Propylene Glycol, Water (Eau/Aqua)

QUESTIONS OR COMMENTS:

Call us at 800.497.7749 • M-F 9am -5pm PST or visit our website at www.classicerotica.net